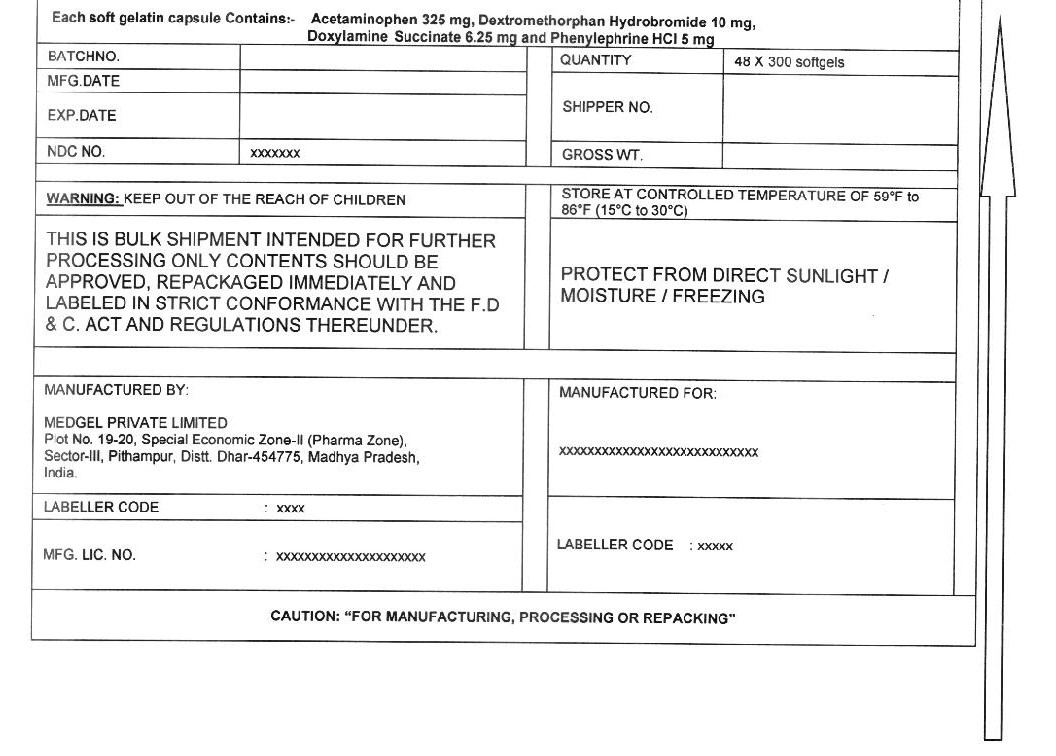 DRUG LABEL: Acetaminophen, Dextromethorphan HBr, Phenylephrine HCl, Doxylamine Succinate
NDC: 55629-016 | Form: CAPSULE, LIQUID FILLED
Manufacturer: ONE2ZEE LIMITED LIABILITY COMPANY
Category: otc | Type: HUMAN OTC DRUG LABEL
Date: 20230325

ACTIVE INGREDIENTS: ACETAMINOPHEN 325 mg/1 1; DEXTROMETHORPHAN HYDROBROMIDE 10 mg/1 1; PHENYLEPHRINE HYDROCHLORIDE 5 mg/1 1; DOXYLAMINE SUCCINATE 6.25 mg/1 1
INACTIVE INGREDIENTS: POLYETHYLENE GLYCOL 400; PROPYLENE GLYCOL; POVIDONE K30; GLYCERIN; SODIUM HYDROXIDE; D&C YELLOW NO. 10; FD&C BLUE NO. 1; TITANIUM DIOXIDE; GELATIN; SORBITOL; WATER

Nighttime Severe Cold and Flu capsule, liquid filled (Acetaminophen 325mg, Dextromethorphan HBr 10mg, Phenylephrine HCl 5mg, Doxylamine Succinate 6.25 mg)

Active ingredients (in each capsule)

Acetaminophen 325 mg

Dextromethorphan HBr 10 mg

Phenylephrine Hydrochloride 5 mg

Doxylamine Succinate 6.25 mg

Purpose

Pain reliever/ fever reducer

Cough suppressant

Antihistamine

Nasal decongestant

Uses

- temporarily relieves common cold/flu symptoms:

ο nasal congestion
ο sinus congestion & pressure
ο cough due to minor throat & bronchial irritation
ο minor aches & pains
ο headache
ο fever
ο sore throat

- reduces swelling of nasal passages
- temporarily restores freer breathing through the nose
- promotes nasal and/or sinus drainage
- helps loosen phlegm (mucus) and thin bronchial secretions to rid the bronchial passageways of bothersome mucus and make coughs more productive.

Warning

Liver warning

This product contains acetaminophen. Severe liver damage may occur if you take

- more than 10 softgels in 24 hours, which is the maximum daily amount for this product
- with other drugs containing acetaminophen
- 3 or more alcoholic drinks every day while using this product

Sore throat warning

If sore throat is severe, persists for more than 2 days, is accompanied or followed by fever, headache, rash, nausea, or vomiting, consult a doctor promptly.

Do not use to sedate children.

Do not use

- with any other drug containing acetaminophen (prescription or nonprescription). If you are not sure whether a drug contains acetaminophen, ask a doctor or pharmacist.
- if you are now taking a prescription monoamine oxidase inhibitor (MAOI) (certain drugs for depression, psychiatric, or emotional conditions, or Parkinson's disease), or for 2 weeks after stopping the MAOI drug. If you do not know if your prescription drug contains an MAOI, ask a doctor or pharmacist before taking this product.
- if you have ever had an allergic reaction to this product or any of its ingredients
- in children under 12 years of age

Ask a doctor before use if you have

- liver disease
- heart disease
- high blood pressure
- thyroid disease
- diabetes
- glaucoma
- cough with excessive phlegm (mucus)
- a breathing problem such as emphysema or chronic bronchitis
- difficulty in urination due to enlargement of the prostate gland
- persistent or chronic cough such as occurs with smoking, asthma, or emphysema

When using this product

- do not exceed recommended dosage
- may cause marked drowsiness
- avoid alcoholic drinks
- alcohol, sedatives, and tranquilizers may increase drowsiness
- be careful when driving a motor vehicle or operating machinery
- excitability may occur, especially in children

Stop use and ask a doctor if

- pain, cough, or nasal congestion gets worse or lasts more than 7 days
- fever gets worse or lasts more than 3 days
- redness or swelling is present
- new symptoms occur
- cough comes back or occurs with rash or headache that lasts.

These could be signs of a serious condition.

- nervousness, dizziness, or sleeplessness occurs

If pregnant or breast-feeding, ask a health professional before use.

Keep out of reach of children. In case of overdose, get medical help or contact a Poison Control Center right away. Quick medical attention is critical for adults as well as for children even if you do not notice any signs or symptoms.

Overdose warning:

Taking more than directed can cause serious health problems. In case of overdose, get medical help or contact a Poison Control Center right away. Quick medical attention is critical for adults as well as for children even if you do not notice any signs or symptoms.

Direction

- take only as directed - see Overdose warning
- do not exceed 4 doses per 24 hours

adults & children 12 years of age and over | 2 softgels with water every 4 hours
Children under 12 years of age | ask a doctor

When using other Nighttime or Daytime products, carefully read each label to ensure correct dosing

Other Information:

- store at room temperature 59°-86°F (15°-30°C)

Inactive ingredients

polyethylene glycol 400, propylene glycol, povidone k30, sodium hydroxide, FD&C blue #1, D&C yellow #10, titanium dioxide, gelatin, glycerin, sorbitol, water

PRINCIPAL DISPLAY PANEL - Shipping Label

Acetaminophen, Dextromethorphan HBr, Phenylephrine HCL, Doxylamine Succinate capsules

Each Softgel Contains:
(Acetaminophen USP 325 mg, Dextromethorphan Hydrobromide USP 10 mg, Phenylephrine Hydrochloride USP 5mg, Doxylamine Succinate 6.25 mg)

LOT NO:
DRUM NO:
MFG DATE:
QUANTITY:
NDC NO: 55629-016-
EXP DATE:

WARNING:
KEEP OUT OF REACH OF CHILDREN

STORE CONTROLLED ROOM TEMPERATURE OF 59° - 86°F (15° - 30°C)
PROTECT FROM LIGHT, MOISTURE AND FREEZING

THIS IS A BULK SHIPMENT INTENDED FOR FURTHER PROCESSING ONLY.

CONTENTS SHOULD BE APPROVED, REPACKAGED IMMEDIATELY AND LABELED IN STRICT CONFORMANCE WITH
THE F.D & C.ACT AND REGULATIONS THEREUNDER.